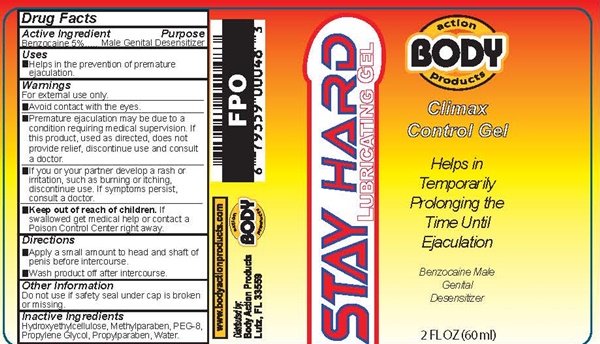 DRUG LABEL: STAY HARD
NDC: 70742-048 | Form: GEL
Manufacturer: Product Max Group Inc
Category: otc | Type: HUMAN OTC DRUG LABEL
Date: 20160807

ACTIVE INGREDIENTS: BENZOCAINE 2833 mg/60 mL
INACTIVE INGREDIENTS: HYDROXYETHYL CELLULOSE (140 MPA.S AT 5%); METHYLPARABEN; POLYETHYLENE GLYCOL 400; PROPYLENE GLYCOL; PROPYLPARABEN; WATER

STAY HARD - 048

Drug Facts Active Ingredient

Benzocaine 5%

Purpose

Male Genital Desensitizer

Keep out of reach of children

If swallowed get medical help or contact a Poison Control Center right away.

Uses

- Helps in the prevention of premature ejaculation.

Warnings

For external use only.

- Avoid contact with the eyes.
- Premature ejaculation may be due to a condition requiring medical supervision. If this product, used as directed, does not provide relief, discontinue use and consult a doctor.
- If you or your partner develop a rash or irritation, such as burning or itching, discontinue use. If symptoms persist, consult a doctor.

Directions

- Apply a small amount to head and shaft of penis before intercourse.
- Wash product off after intercourse.

Other Information

Do not use if safety seal under cap is broken or missing.

Inactive Ingredients

Hydroxyethylcellulose, Methylparaben, PEG-8, Propylene Glycol, Propylparaben, Water

STAY HARD product Label

STAY HARD
LUBRICATING GEL

ACTION BODY PRODUCTS

Climax Control gel

Helps in Temporarily Prolonging the Time Until Ejaculation

Benzocaine Male Genital desensitizer

2 FL OZ (60 ml)

www.bodyaction products.com

Distributed by:

Body Action Products

Lutz, FL 33559